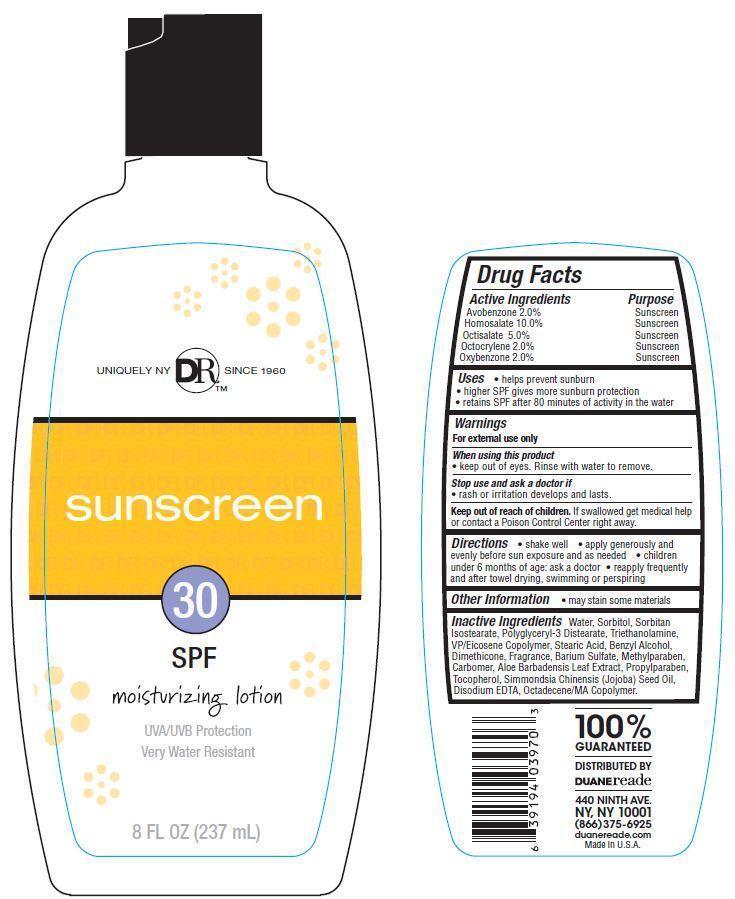 DRUG LABEL: Duane Reade Sunscreen
NDC: 67732-414 | Form: LOTION
Manufacturer: DUANE READE INC.
Category: otc | Type: HUMAN OTC DRUG LABEL
Date: 20121114

ACTIVE INGREDIENTS: AVOBENZONE 2 g/100 g; HOMOSALATE 10 g/100 g; OCTISALATE 5 g/100 g; OCTOCRYLENE 2 g/100 g; OXYBENZONE 2 g/100 g
INACTIVE INGREDIENTS: WATER; SORBITOL; STEARIC ACID; TROLAMINE; BENZYL ALCOHOL; BARIUM SULFATE; DIMETHICONE; ALOE VERA LEAF; METHYLPARABEN; PROPYLPARABEN; TOCOPHEROL; EDETATE DISODIUM; JOJOBA OIL

Drug Facts

Active Ingredients

Avobenzone 2.0 %

Homosalate 10.0%

Octisalate 5.0%

Octocrylene 2.0%

Oxybenzone 2.0%

Purpose

Sunscreen

Uses

- helps prevent sunburn
- higher SPF gives more sunburn protection
- retains SPF after 80 minutes of activity in the water

Warnings

For external use only

When using this product

- keep out of eyes. Rinse with water to remove.

stop use and ask a doctor if

- rash or irritation develops and lasts

keep out of the reach of children

If swallowed get medical help or contact a poison control center right away.

Directions

- shake well
- apply generously and evenly before sun exposure and as needed
- children under 6 months of age:ask a doctor
- reapply frequently and after towel drying, swimming or perspiring

Other Information

- may stain some materials

Inactive Ingredients

Water, Sorbitan Isostearate, Sorbitol, Polyglyceryl-3 Distearate, Triethanolamine, Stearic Acid, VP/Eicosene Copolymer, Benzyl Alcohol, Dimethicone, Barium Sulfate, Carbomer, Simmondsia Chinensis (Jojoba) Seed Oil, Tocopherol, Disodium EDTA, Octadecene/MA Copolymer, Aloe Barbadensis Leaf Extract, Methylparaben, Propylparaben, Fragrance.

Principal Display Panel

UNIQUELY NY DRTM SINCE 1960
sunscreen
30
SPF
moisturizing lotion
UVA/UVB Protection
Very Water Resistant
8 FL OZ (237mL)